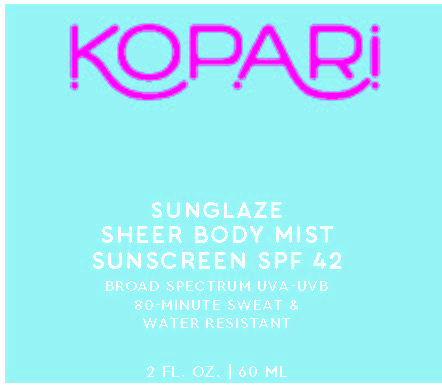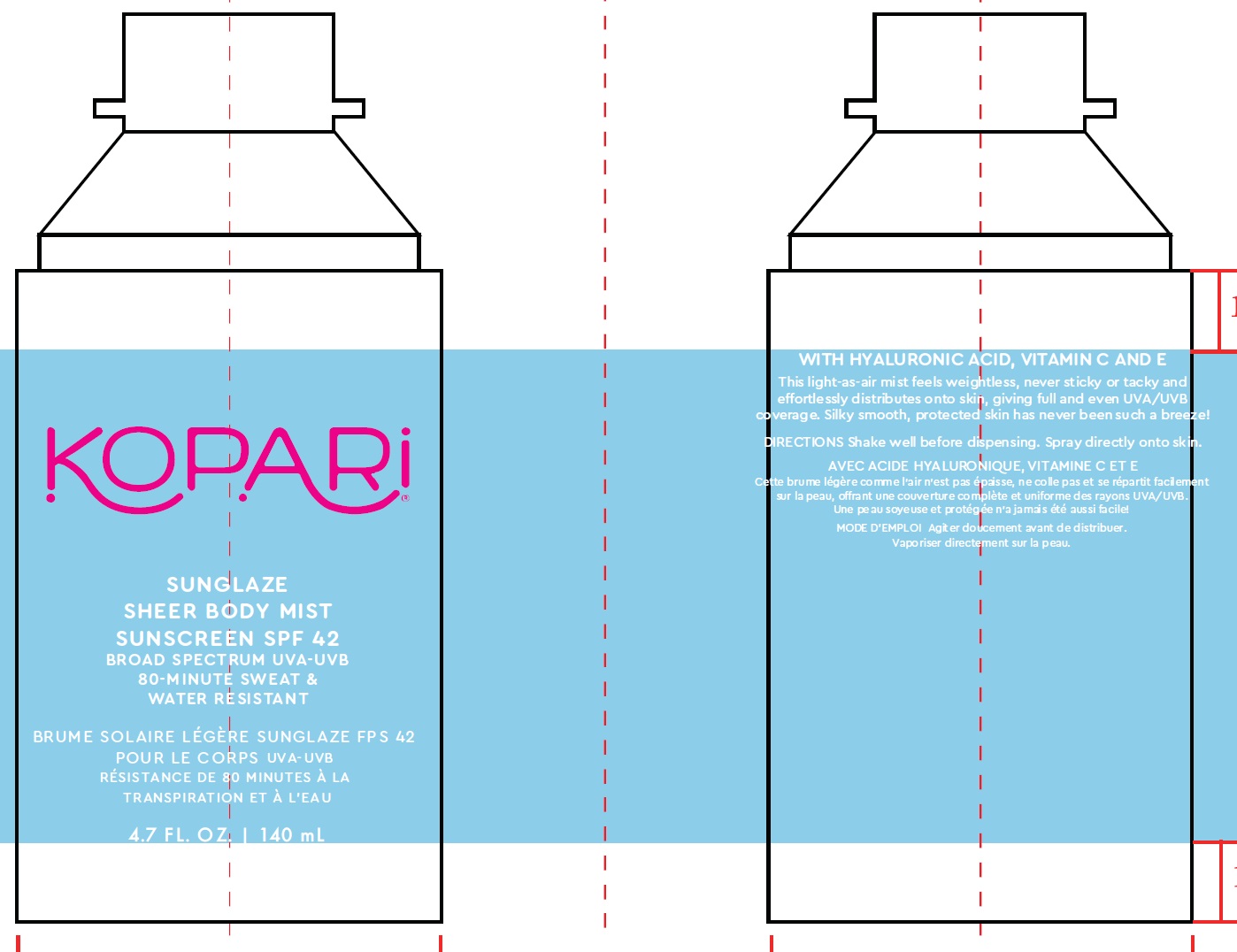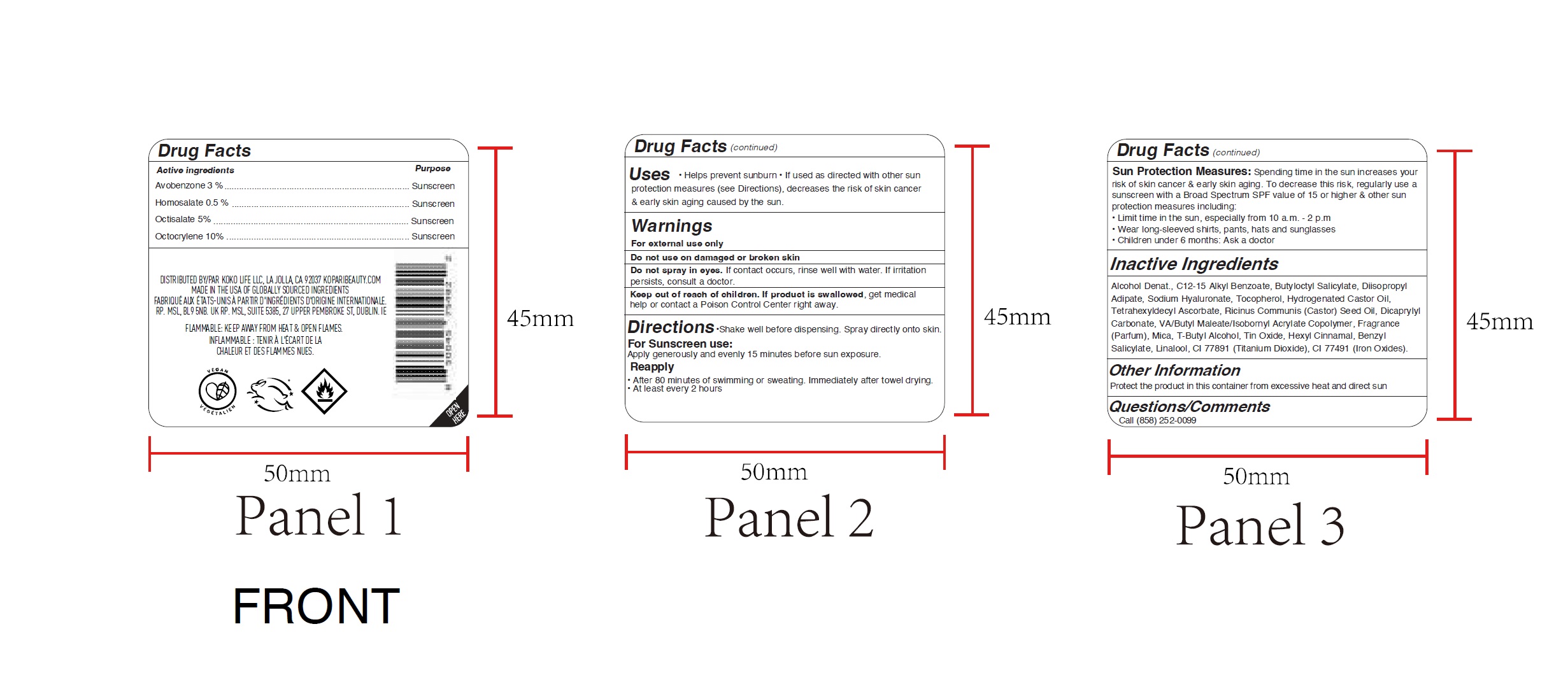 DRUG LABEL: Kopari Sunglaze Sheer Body Mist Sunscreen SPF42
NDC: 84130-000 | Form: SPRAY
Manufacturer: Kopari Beauty
Category: otc | Type: HUMAN OTC DRUG LABEL
Date: 20251214

ACTIVE INGREDIENTS: AVOBENZONE 30 mg/1 mL; HOMOSALATE 5 mg/1 mL; OCTISALATE 50 mg/1 mL; OCTOCRYLENE 100 mg/1 mL
INACTIVE INGREDIENTS: ALCOHOL; ALKYL (C12-15) BENZOATE; BUTYLOCTYL SALICYLATE; DIISOPROPYL ADIPATE; HYALURONATE SODIUM; TOCOPHEROL; HYDROGENATED CASTOR OIL; TETRAHEXYLDECYL ASCORBATE; CASTOR OIL; DICAPRYLYL CARBONATE; DIBUTYL MALEATE; MICA; TERT-BUTYL ALCOHOL; STANNIC OXIDE; .ALPHA.-HEXYLCINNAMALDEHYDE; BENZYL SALICYLATE; LINALOOL, (+/-)-; TITANIUM DIOXIDE; FERRIC OXIDE RED

Kopari Sunglaze Sheer Body Mist Sunscreen SPF42

Active ingredients

Avobenzone 3 %
Homosalate 0.5 %
Octisalate 5%
Octocrylene 10%

Purpose

Sunscreen

Uses

- Helps prevent sunburn
- If used as directed with other sun protection measures (see Directions), decreases the risk of skin cancer & early skin aging caused by the sun.

Warnings

For external use only

Do not use

on damaged or broken skin Do not spray in eyes.If contact occurs, rinse well with water. If irritation persists, consult a doctor.

Keep out of reach of children.

If product is swallowed,get medical help or contact a Poison Control Center right away.

Directions

- Shake well before dispensing. Spray directly onto skin. For Sunscreen use:Apply generously and evenly 15 minutes before sun exposure. Reapply
- After 80 minutes of swimming or sweating. Immediately after towel drying.
- At least every 2 hours

Sun Protection Measures:

Spending time in the sun increases your

risk of skin cancer & early skin aging. To decrease this risk, regularly use a

sunscreen with a Broad Spectrum SPF value of 15 or higher & other sun

protection measures including:

- Limit time in the sun, especially from 10 a.m. - 2 p.m
- Wear long-sleeved shirts, pants, hats and sunglasses
- Children under 6 months: Ask a doctor

Inactive Ingredients

Alcohol Denat., C12-15 Alkyl Benzoate, Butyloctyl Salicylate, Diisopropyl Adipate, Sodium Hyaluronate, Tocopherol, Hydrogenated Castor Oil, Tetrahexyldecyl Ascorbate, Ricinus Communis (Castor) Seed Oil, Dicaprylyl Carbonate, VA/Butyl Maleate/Isobornyl Acrylate Copolymer, Fragrance (Parfum), Mica, T-Butyl Alcohol, Tin Oxide, Hexyl Cinnamal, Benzyl Salicylate, Linalool, CI 77891 (Titanium Dioxide), CI 77491 (Iron Oxides).

Other Information

Protect the product in this container from excessive heat and direct sun

Questions/Comments

Call (858) 252-0099